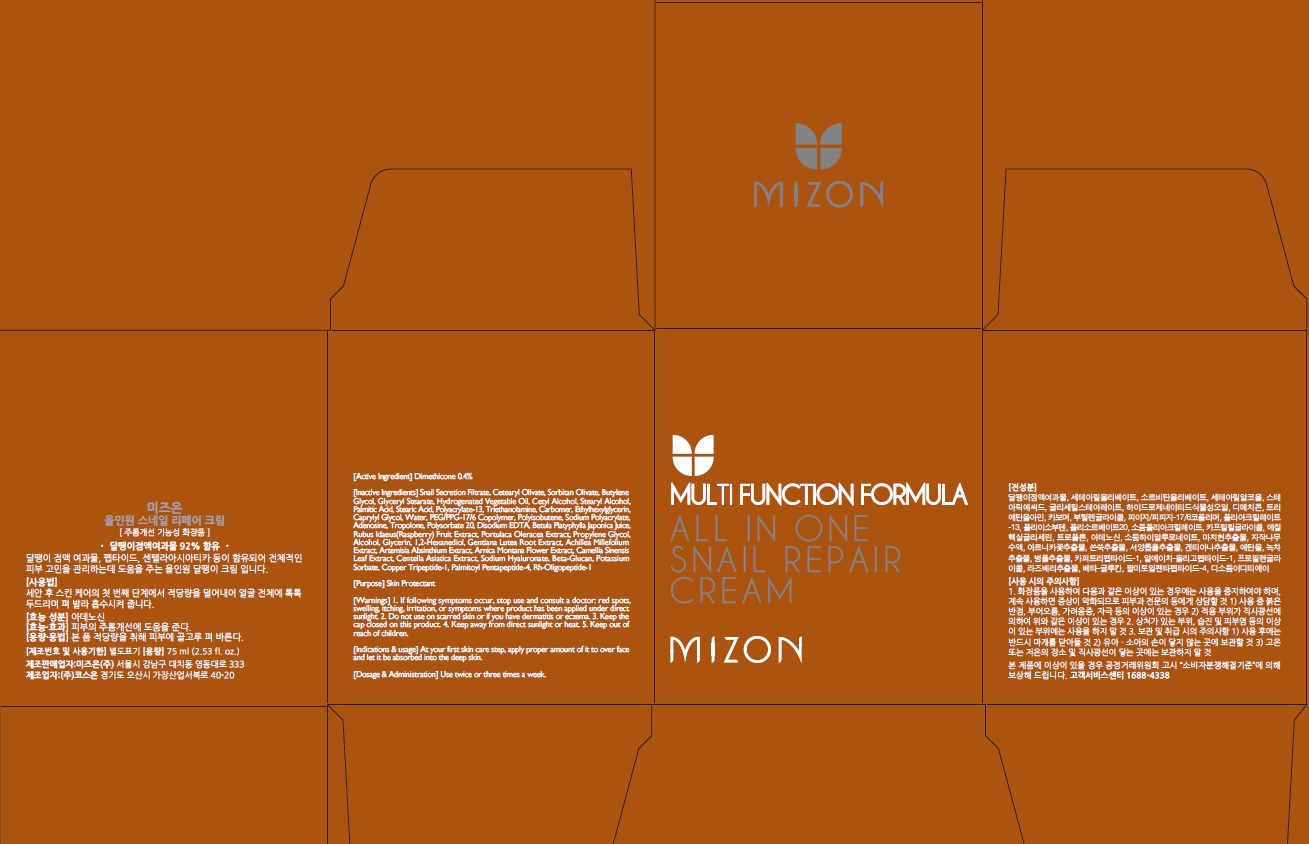 DRUG LABEL: MIZON ALL IN ONE SNAIL REPAIR
NDC: 57718-130 | Form: CREAM
Manufacturer: MIZON CO., LTD.
Category: otc | Type: HUMAN OTC DRUG LABEL
Date: 20160530

ACTIVE INGREDIENTS: Dimethicone 0.3 g/75 mL
INACTIVE INGREDIENTS: Cetearyl Olivate; Sorbitan Olivate

ACTIVE INGREDIENT

Active Ingredient: Dimethicone 0.4%

INACTIVE INGREDIENT

Inactive Ingredients: Snail Secretion Filtrate, Cetearyl Olivate, Sorbitan Olivate, Butylene Glycol, Glyceryl Stearate, Hydrogenated Vegetable Oil, Cetyl Alcohol, Stearyl Alcohol, Palmitic Acid, Stearic Acid, Polyacrylate-13, Triethanolamine, Carbomer, Ethylhexylglycerin, Caprylyl Glycol, Water, PEG/PPG-17/6 Copolymer, Polyisobutene, Sodium Polyacrylate, Adenosine, Tropolone, Polysorbate 20, Disodium EDTA, Betula Platyphylla Japonica Juice, Rubus Idaeus(Raspberry) Fruit Extract, Portulaca Oleracea Extract, Propylene Glycol, Alcohol, Glycerin, 1,2-Hexanediol, Gentiana Lutea Root Extract, Achillea Millefolium Extract, Artemisia Absinthium Extract, Arnica Montana Flower Extract, Camellia Sinensis Leaf Extract, Centella Asiatica Extract, Sodium Hyaluronate, Beta-Glucan, Potassium Sorbate, Copper Tripeptide-1, Palmitoyl Pentapeptide-4, Rh-Oligopeptide-1

PURPOSE

Purpose: Skin Protectant

WARNINGS

Warnings: 1. If following symptoms occur, stop use and consult a doctor: red spots, swelling, itching, irritation, or symptoms where product has been applied under direct sunlight. 2. Do not use on scarred skin or if you have dermatitis or eczema. 3. Keep the cap closed on this product. 4. Keep away from direct sunlight or heat. 5. Keep out of reach of children.

KEEP OUT OF REACH OF CHILDREN

INDICATIONS & USAGE

Indications & usage: At your first skin care step, apply proper amount of it to over face and let it be absorbed into the deep skin.

DOSAGE & ADMINISTRATION

Dosage & Administration: Use twice or three times a week.